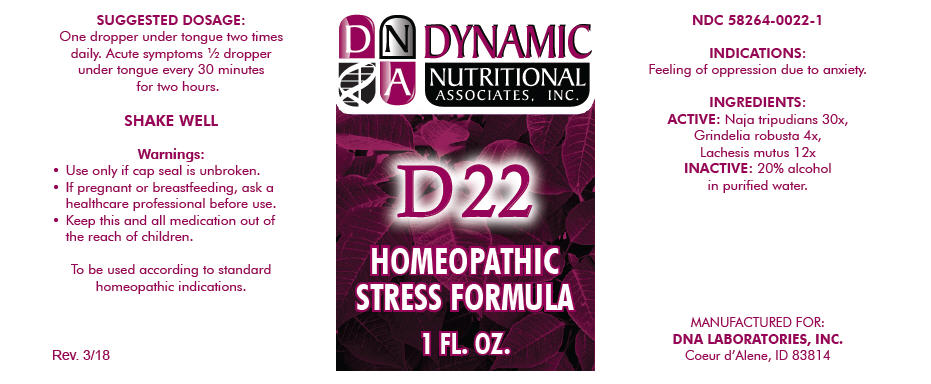 DRUG LABEL: D-22
NDC: 58264-0022 | Form: SOLUTION/ DROPS
Manufacturer: DNA Labs, Inc.
Category: homeopathic | Type: HUMAN OTC DRUG LABEL
Date: 20250113

ACTIVE INGREDIENTS: NAJA NAJA VENOM 30 [hp_X]/1 mL; GRINDELIA HIRSUTULA FLOWERING TOP 4 [hp_X]/1 mL; LACHESIS MUTA VENOM 12 [hp_X]/1 mL
INACTIVE INGREDIENTS: ALCOHOL; WATER

D-22

NDC 58264-0022-1

INDICATIONS

PURPOSE

Feeling of oppression due to anxiety.

INGREDIENTS

ACTIVE

Naja tripudians 30x, Grindelia robusta 4x, Lachesis mutus 12x

INACTIVE

20% alcohol in purified water.

SUGGESTED DOSAGE

One dropper under tongue two times daily. Acute symptoms ½ dropper under tongue every 30 minutes for two hours.

STORAGE AND HANDLING

SHAKE WELL

Warnings

- Use only if cap seal is unbroken.

PREGNANCY OR BREAST FEEDING

- If pregnant or breastfeeding, ask a healthcare professional before use.

KEEP OUT OF REACH OF CHILDREN

- Keep this and all medication out of the reach of children.

To be used according to standard homeopathic indications.

PRINCIPAL DISPLAY PANEL - 1 FL. OZ. Bottle Label

DYNAMIC
NUTRITIONAL
ASSOCIATES, INC.

D 22

HOMEOPATHIC
STRESS FORMULA

1 FL. OZ.